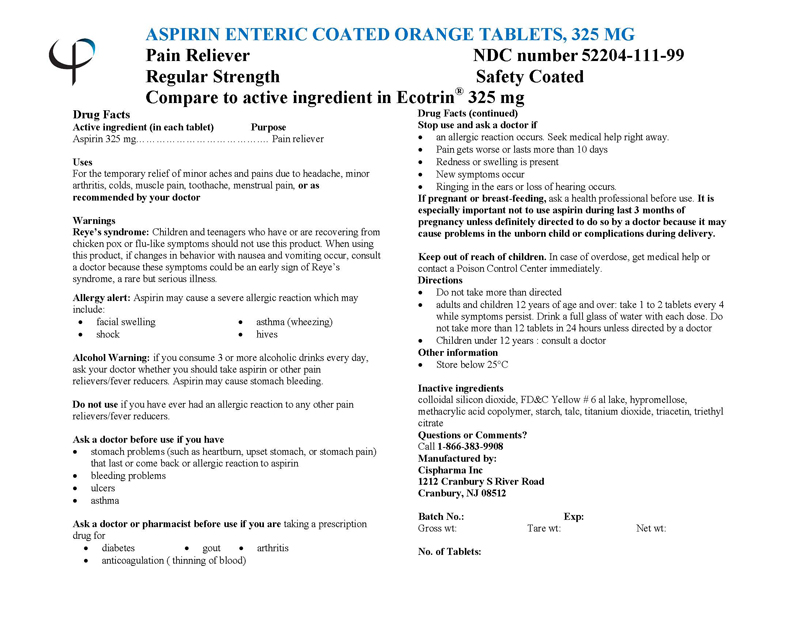 DRUG LABEL: ASPIRIN
NDC: 52204-111 | Form: TABLET, COATED
Manufacturer: Cispharma, Inc
Category: otc | Type: HUMAN OTC DRUG LABEL
Date: 20110417

ACTIVE INGREDIENTS: ASPIRIN 325 mg/1 1
INACTIVE INGREDIENTS: SILICON DIOXIDE; HYPROMELLOSE 2910 (5 MPA.S); FD&C YELLOW NO. 6; METHACRYLIC ACID - ETHYL ACRYLATE COPOLYMER (1:1) TYPE A; STARCH, CORN; TALC; TITANIUM DIOXIDE; TRIACETIN; TRIETHYL CITRATE

ASPIRIN ENTERIC COATED ORANGE TABLETS, 325 mg

Drug Facts

Active ingredient (in each tablet)

Aspirin (NSAID*) .............................. 325 mg

PURPOSE

Pain Reliever

Uses

For the temporary relief of minor aches and pains due to headache, minor arthritis, colds, muscle pain, toothache, menstrual pain, or as recommended by your doctor

Warnings

Reye's syndrome: Children and teenagers who have or are recovering from chicken pox or flu-like symptoms should not use this product. When using this product, if changes in behavior with nausea and vomiting occur, consult a doctor because these symptoms could be an early sign of Reye's syndrome, a rare but serious illness.

Allergy alert: Aspirin may cause a severe allergic reaction which may include:

- facial swelling
- asthma (wheezing)
- shock
- hives

Alcohol Warning: if you consume 3 or more alcoholic drinks every day, ask your doctor whether you should take aspirin or other pain relievers/fever reducers. Aspirin may cause stomach bleeding.

Do not use if you have ever had an allergic reaction to any other pain relievers/fever reducers.

Ask a doctor before use if you have

- stomach problems (such as heartburn, upset stomach, or stomach pain) that last or come back or allergic reaction to aspirin
- bleeding problems
- ulcers
- asthma

Ask a doctor or pharmacist before use if you are taking a prescription drug for

- diabetes
- gout
- arthritis
- anticoagulation (thinning of blood)

INDICATIONS AND USAGE

Indicated for pain relief.

Stop use and ask a doctor if

- An allergic reaction occurs. Seek medical help right away
- Pain gets worse or lasts more than 10 days
- Redness or swelling is present
- New symptoms occur
- Ringing in the ears or loss of hearing occurs.

PREGNANCY OR BREAST FEEDING

If pregnant or breast-feeding, ask a health professional before use. It is especially important not to use aspirin during last 3 months of pregnancy unless definitely directed to do so by a doctor because it may cause problems in the unborn child or complications during delivery.

Keep out of reach of children.

OVERDOSAGE

In case of overdose, get medical help or contact a Poison Control Center immediately.

Directions:

- Do not take more than directed
- Adults and children 12 years of age and over: take 1 to 2 tablets every 4 while symptoms persist. Drink a full glass of water with each dose. Do not take more than 12 tablets in 24 hours unless directed by a doctor
- Children under 12 years: consult a doctor

Other Information

- Store below 25°C

Inactive Ingredients

colloidal silicon dioxide, FD&C Yellow # 6 al lake, hypromellose, methacrylic acid copolymer, starch, talc, titanium dioxide, triacetin, triethyl citrate

Questions or Comments?
Call 1-866-383-9908

Manufactured by:

Cispharma Inc
1212 Cranbury S River Road
Cranbury, NJ 08512